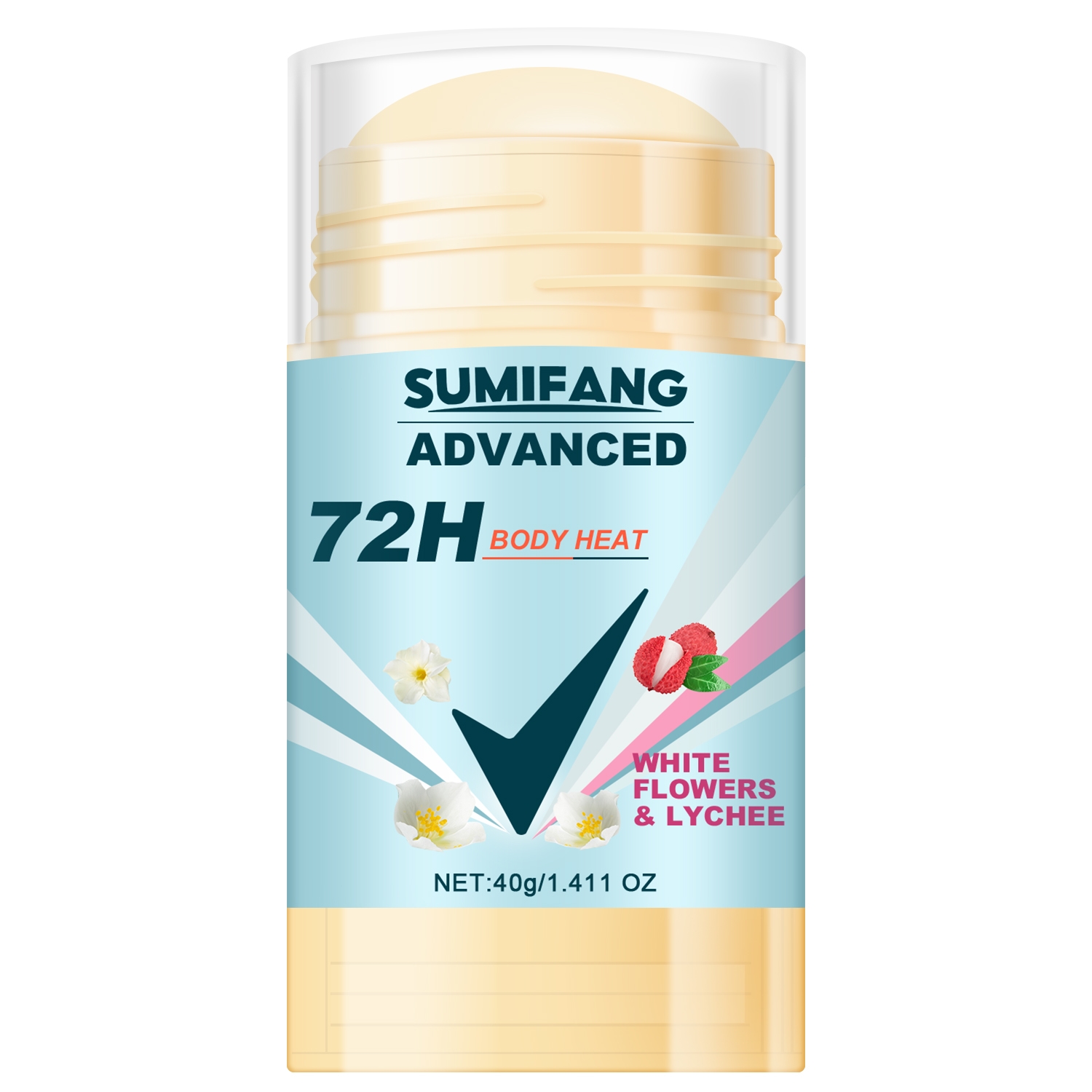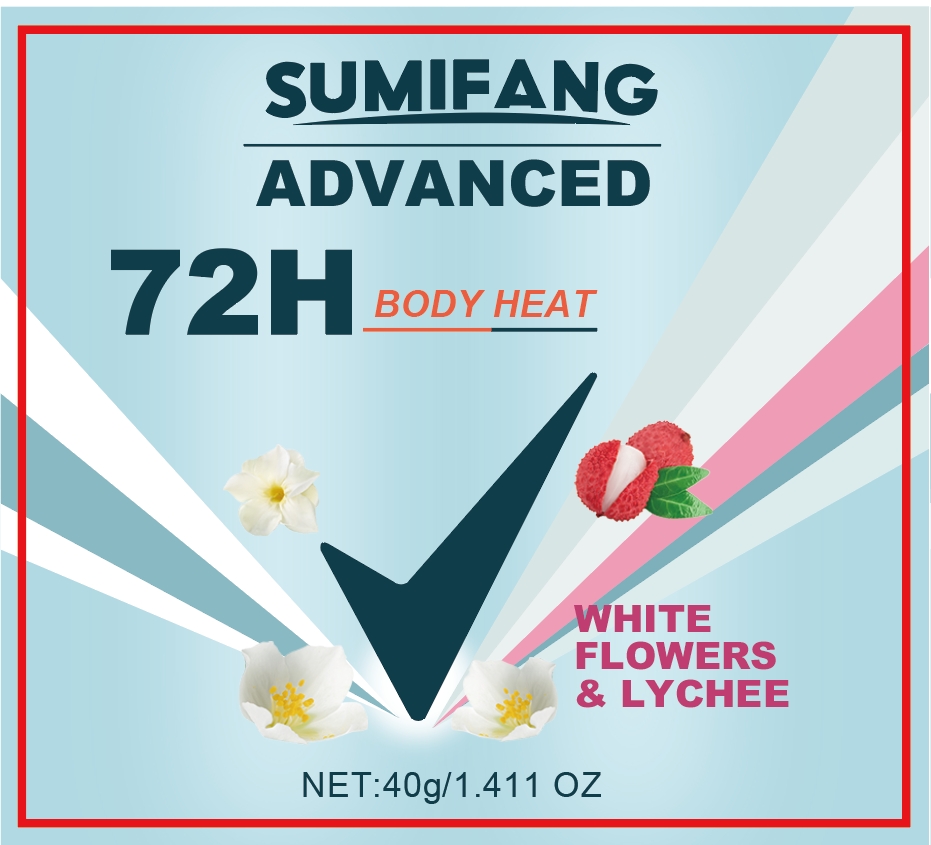 DRUG LABEL: 72H BODYHEAT
NDC: 84025-125 | Form: STICK
Manufacturer: Guangzhou Yanxi Biotechnology Co.. Ltd
Category: otc | Type: HUMAN OTC DRUG LABEL
Date: 20240807

ACTIVE INGREDIENTS: MINERAL OIL 5 mg/40 g
INACTIVE INGREDIENTS: WATER

DOSAGE AND ADMINISTRATION

Stick for removing men's body odor

WARNINGS

Keep out of children

INACTIVE INGREDIENT

Aqua

INDICATIONS AND USAGE

Applicable to the body odor problems encountered by men in daily life

Keep out of children

PURPOSE

Effectively suppresses men's body odor